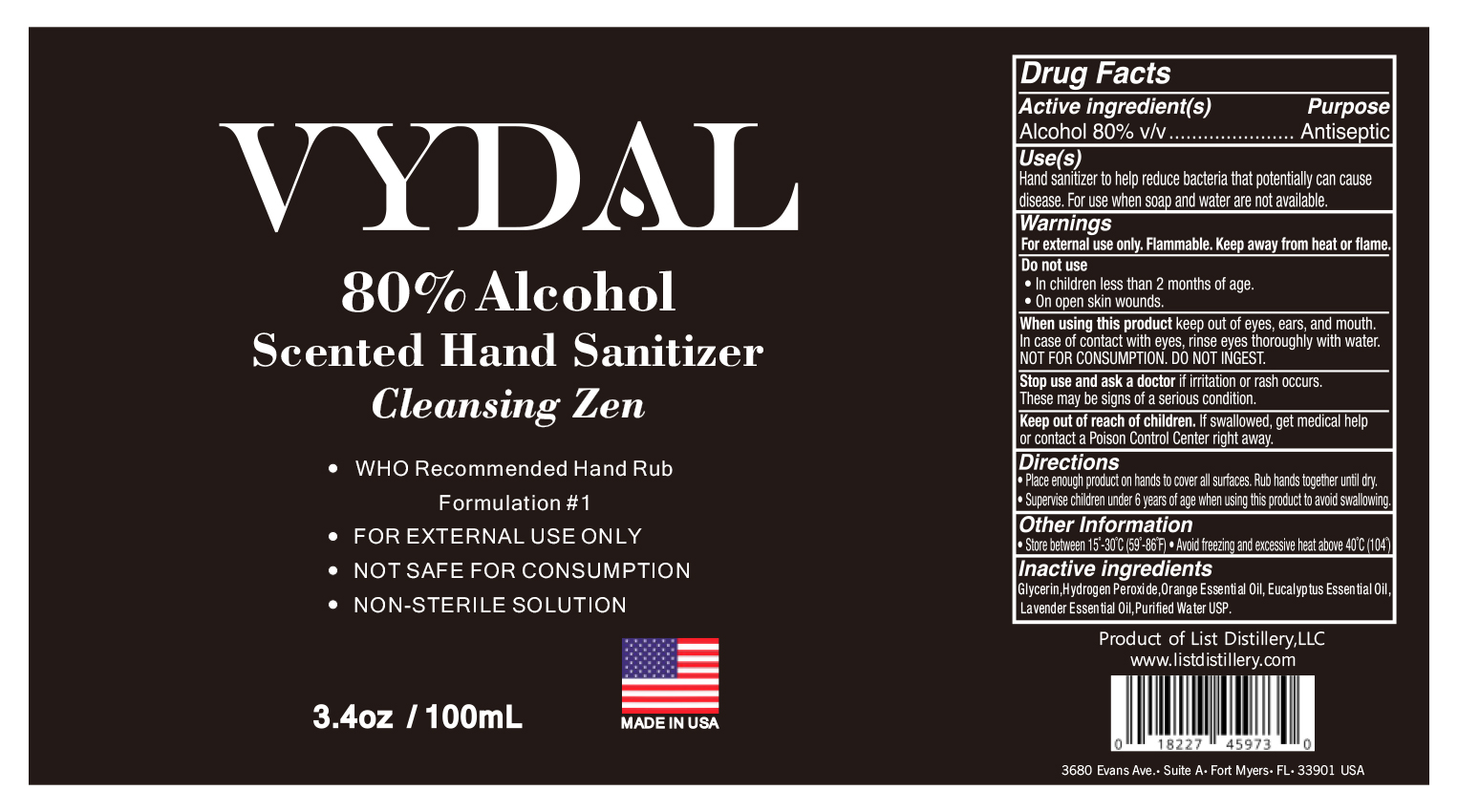 DRUG LABEL: VYDAL Scented Hand Sanitizer
NDC: 74563-003 | Form: LIQUID
Manufacturer: List Distillery, LLC
Category: otc | Type: HUMAN OTC DRUG LABEL
Date: 20200615

ACTIVE INGREDIENTS: ALCOHOL 800 mL/1000 mL
INACTIVE INGREDIENTS: ENGLISH LAVENDER OIL; ORANGE OIL; EUCALYPTUS OIL; WATER 184.2 mL/1000 mL; GLYCEROL FORMAL 14.5 mL/1000 mL; HYDROGEN PEROXIDE 1.3 mL/1000 mL

Active Ingredient [s] Purpose

Alcohol 80% v/v.......................................Antiseptic

Do not use

- In children under 2 months of age.
- On open skin wounds.

Keep out of reach of children. If swallowed, get medical help or contact a Poison Control Center right away.

Stop use and ask a doctor if irritation or rash occurs. These may be signs of a serious condition.

Warnings

For external use only. Flammable. Keep away from heat or flame.

When using this product keep out of eyes, ears, and mouth. In case of contact with eyes, rinse eyes thoroughly with water. NOT FOR CONSUMPTION. DO NOT INGEST.

Other Information

- Store between 15°-30°C (59°-86°F)
- Avoid freezing and excessive heat above 40°C (104°)

Inactive Ingredients

Gylcerin, Hydrogen Peroxide, Orange Oil, Eucalyptus Oil, English Lavender Oil, Purified Water USP

Directions

- Place enough product on hands to cover all surfaces. Rub hands together until dry.
- Supervise children under 6 years of age when using this product to avoid swallowing.

INDICATIONS AND USAGE

Use [s]

- Hand sanitizer to help reduce bacteria that potentially can cause disease.
- For use when soap and water are not available.

RECENT MAJOR CHANGES

Use [s]

Hand sanitizer to help reduce bacteria that potentially can cause disease.
For use when soap and water are not available.

PURPOSE

Use [s]

- Hand sanitizer helps reduce bacteria that potentially causes disease.
- For use when soap and water are not available.

PACKAGE LABEL

VYDAL

80% Alcohol

Scented Hand Sanitizer

Cleansing Zen

- WHO Rocommended Hand Rub

Formulation #1

- FOR EXTERNAL USE ONLY
- NOT SAFE FOR CONSUMPTION
- NON-STERILE SOLUTION

3.4 fl oz/100 mL

MADE IN USA